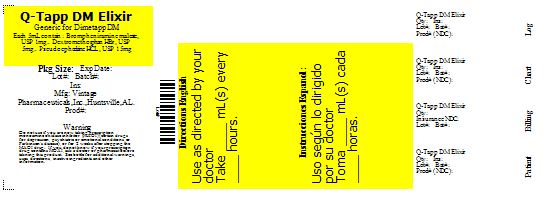 DRUG LABEL: Q-Tapp DM Elixir
                        
NDC: 68788-0852 | Form: ELIXIR
Manufacturer: Preferred Pharmaceuticals, Inc
Category: otc | Type: HUMAN OTC DRUG LABEL
Date: 20110510

ACTIVE INGREDIENTS: Brompheniramine maleate 1 mg/5 mL; Pseudoephedrine hydrochloride 15 mg/5 mL; Dextromethorphan hydrobromide 5 mg/5 mL
INACTIVE INGREDIENTS: anhydrous citric acid; FD&C blue no. 1; FD&C red no. 40; glycerin; propylene glycol; saccharin sodium; sodium benzoate; sodium citrate; sorbitol; water

Q-Tapp DM Elixir

Active Ingredient: Brompheniramine maleate 1 mg (in each 5 mL = 1 tsp)

Active Ingredient: Pseudoephedrine hydrochloride 15 mg (in each 5 mL = 1 tsp)

Active Ingredient: Dextromethorphan hydrobromide 5 mg (in each 5 mL = 1 tsp)

Purpose of Brompheniramine maleate: Antihistamine

Purpose of Pseudoephedrine hydrochloride: Nasal Decongestant

Purpose of Dextromethorphan hydrobromide: Cough Suppressant

Uses

- temporarily relieves cough due to minor throat and bronchial irritation occurring with a cold, and nasal congestion due to the common cold, hay fever or other upper respiratory allergies, or associated with sinusitis
- temporarily relieves symptoms due to hay fever (allergic rhinitis):
-
  - runny nose
  - sneezing
  - itchy, watery eyes
  - itching of the nose or throat
  - temporarily restores freer breathing through the nose

Warnings

Do not use in children under 6 years of age

Do not use if you are now taking a prescription monoamine oxidase inhibitor (MAOI) (certain drugs for depression, psychiatric or emotional conditions, or Parkinson’s disease), or for 2 weeks after stopping the MAOI drug. If you do not know if your prescription drug contains an MAOI, ask a doctor or pharmacist before taking this product.

Ask a doctor before use if you have

- heart disease
- high blood pressure
- thyroid disease
- diabetes
- glaucoma
- trouble urinating due to an enlarged prostate gland
- cough that occurs with too much phlegm (mucus)
- a breathing problem or persistent or chronic cough that lasts or as occurs with smoking, asthma, emphysema, or chronic bronchitis

Ask a doctor or pharmacist before use if you are taking sedatives or tranquilizers

When using this product

- do not use more than directed
- marked drowsiness may occur
- avoid alcoholic beverages
- alcohol, sedatives, and tranquilizers may increase drowsines
- be careful when driving a motor vehicle or operating machinery
- excitability may occur, especially in children

Stop use and ask a doctor if

- you get nervous, dizzy, or sleepless
- symptoms do not improve within 7 days or are accompanied by fever
- cough lasts more than 7 days, comes back, or is accompanied by fever, rash, or persistent headache. These could be signs of a serious condition.

PREGNANCY OR BREAST FEEDING

If pregnant or breast-feeding, ask a health professional before use.

Keep out of reach of children. In case of overdose, get medical help or contact a Poison Control Center right away.

Directions

- do not take more than 4 doses in any 24-hour

Adults and children 12 years and over | 20 mL (4 tsp) every 4 to 6 hours
Children 6 years to under 12 years | 10 mL (2 tsp) every 4 to 6 hours
Children under 6 years | DO NOT USE

Other information

- each tsp contains: sodium 2 mg
- Store at room temperature 20°-25°C (68°-77°F).

Inactive ingredients

citric acid, FD&C blue no. 1, FD&C red no. 40, glycerin, grape flavor, propylene glycol, saccharin sodium, sodium benzoate, sodium citrate, sorbitol, water.

Questions

Made in USA
for Qualitest Pharmaceuticals
130 Vintage Drive
Huntsville, AL 35811